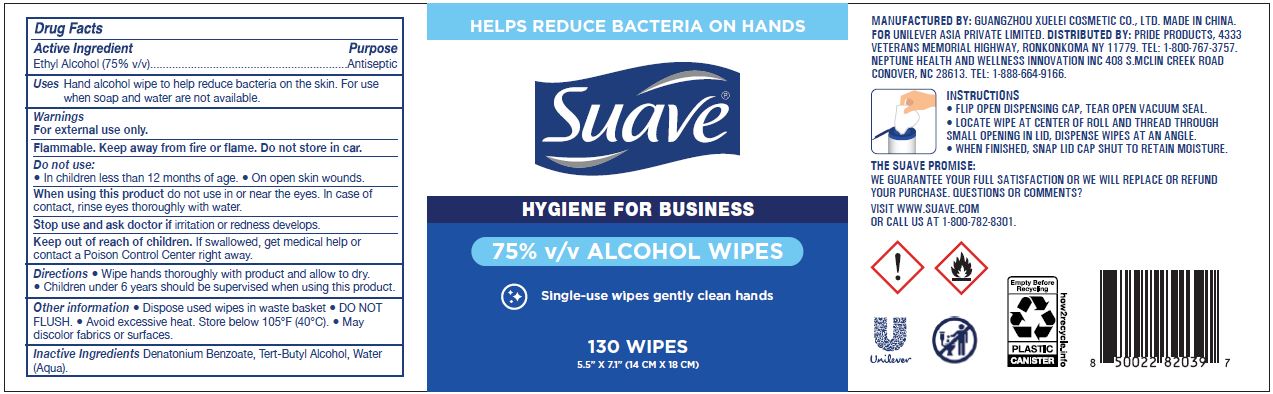 DRUG LABEL: Suave 75% v/v ALCOHOL WIPES
NDC: 50069-113 | Form: SOLUTION
Manufacturer: UNILEVER ASIA PRIVATE LIMITED
Category: otc | Type: HUMAN OTC DRUG LABEL
Date: 20210202

ACTIVE INGREDIENTS: ALCOHOL 7.5 mL/1 1
INACTIVE INGREDIENTS: WATER; DENATONIUM BENZOATE; TERT-BUTYL ALCOHOL

Suave 75% v/v ALCOHOL WIPES

ACTIVE INGREDIENT

Ethyl alcohol (75% v/v)

PURPOSE

ANTISEPTIC

USE

Hand alcohol wipe to help reduce bacteria on the skin. For use when soap and water are not available.

WARNINGS

For External Use only.

Flammable. Keep away from fire or flame. Do not store in car.

Do not use:

- In children less than 12 months of age.
- On open skin wounds.

When using this product do not use in or near the eyes. In case of contact, rinse eyes thoroughly with water

Stop use and ask doctor if irritation or redness develops.

Keep out of reach of children.

If swallowed, get medical help or contact a Poison Control Center right away.

Keep out of reach of children. If swallowed, get medical help or contact a Poison Control Center right away.

DIRECTIONS

- Wipe hands thoroughly with product and allow to dry
- Children under 6 should be supervised when using this product.

OTHER INFORMATION

- Dispose used wipes in waste basket
- DO NOT FLUSH.
- Avoid excessive heat. Store below 105°F (40°C).
- May discolor fabrics or surfaces

INACTIVE INGREDIENTS

Denatonium Benzoate, Tert-Butyl Alcohol, Water (Aqua).